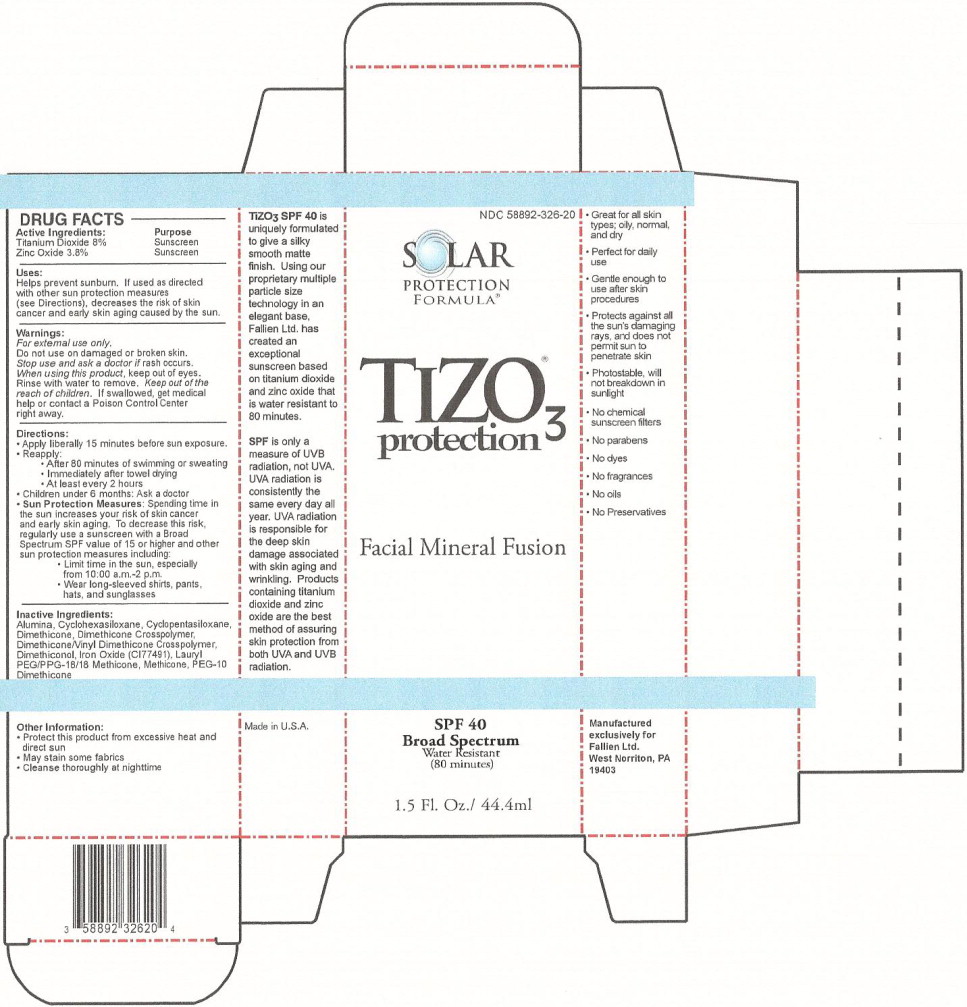 DRUG LABEL: Solar Protection Formula TiZO3 
NDC: 58892-326 | Form: CREAM
Manufacturer: Fallien Cosmeceuticals, LTD.
Category: otc | Type: HUMAN OTC DRUG LABEL
Date: 20121207

ACTIVE INGREDIENTS: Titanium Dioxide 85.4 mg/1 mL; Zinc Oxide 40.7 mg/1 mL
INACTIVE INGREDIENTS: Aluminum Oxide; Cyclomethicone 5; Dimethicone; Ferric Oxide Red

DRUG FACTS

Active Ingredients:

Titanium Dioxide 8%

Zinc Oxide 3.8%

Purpose

Sunscreen

Sunscreen

Uses:

Helps prevent sunburn. If used as directed with other sun protection measures (see Directions), decreases the risk of skin cancer and early skin aging caused by the sun.

Warnings:

For external use only.

Do not use on damaged or broken skin.

Stop use and ask a doctor if rash occurs.

When using this product, keep out of eyes. Rinse with water to remove.

KEEP OUT OF REACH OF CHILDREN

Keep out of the reach of children. If swallowed, get medical help or contact a Poison Control Center right away.

Directions:

- Apply liberally 15 minutes before sun exposure.
- Reapply:
  - After 80 minutes of swimming or sweating
  - Immediately after towel drying
  - At least every 2 hours
- Children under 6 months: Ask a doctor
- Sun Protection Measures: Spending time in the sun increases your risk of skin cancer and early skin aging. To decrease this risk, regularly use a sunscreen with a Broad Spectrum SPF value of 15 or higher and other sun protection measures including:
  - Limit time in the sun, especially from 10:00 a.m.-2 p.m.
  - Wear long-sleeved shirts, pants, hats, and sunglasses

Inactive Ingredients:

Alumina, Cyclohexasiloxane, Cyclopentasiloxane, Dimethicone, Dimethicone Crosspolymer, Dimethicone/Vinyl Dimethicone Crosspolymer, Dimothiconol, Iron Oxide (CI77491), Lauryl PEG/PPG 18/18 Methicone, Methicone, PEG-10 Dimethicone

Other Information:

- Protect this product from excessive heat and direct sun
- May stain some fabrics
- Cleanse thoroughly at nighttime

Principal Display Panel – Carton Label

NDC 58892-326-20

SOLAR
PROTECTION
FORMULA®

TIZO 3® protection

Facial Mineral Fusion

SPF 40
Broad Spectrum
Water Resistant
(80 minutes)

1.5 Fl. Oz./ 44.4 ml